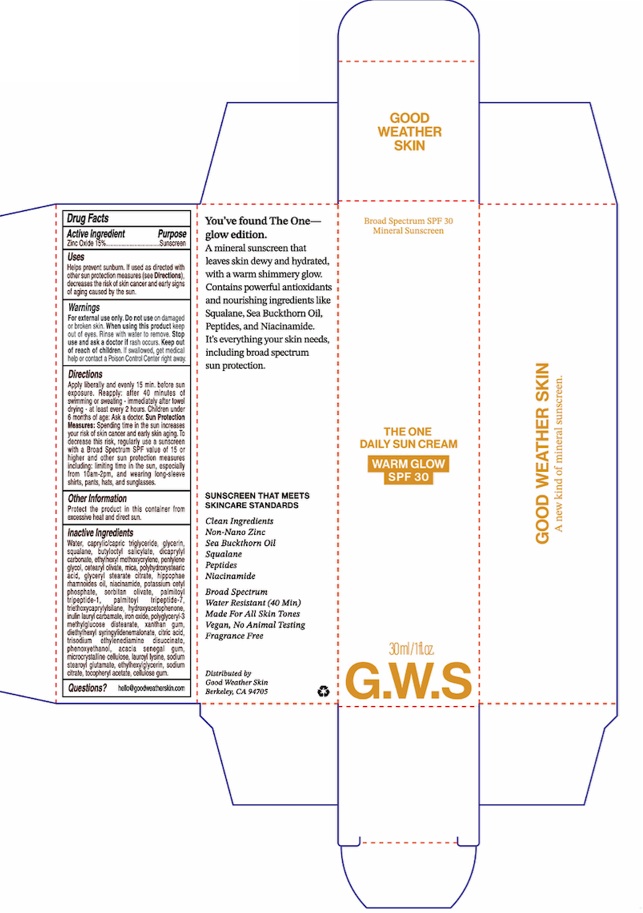 DRUG LABEL: Good Weather Skin The One Daily Sun Warm Glow SPF 30
NDC: 85090-002 | Form: CREAM
Manufacturer: Good Weather Inc.
Category: otc | Type: HUMAN OTC DRUG LABEL
Date: 20250829

ACTIVE INGREDIENTS: ZINC OXIDE 150 mg/1 mL
INACTIVE INGREDIENTS: POLYGLYCERYL-3 METHYLGLUCOSE DISTEARATE; TRISODIUM ETHYLENEDIAMINE DISUCCINATE; LAUROYL LYSINE; DICAPRYLYL CARBONATE; WATER; CAPRYLIC/CAPRIC TRIGLYCERIDE; GLYCERIN; BUTYLOCTYL SALICYLATE; CETEARYL OLIVATE; POLYHYDROXYSTEARIC ACID (2300 MW); GLYCERYL STEARATE CITRATE; SORBITAN OLIVATE; INULIN LAURYL CARBAMATE; MICROCRYSTALLINE CELLULOSE; XANTHAN GUM; SODIUM STEAROYL GLUTAMATE; SODIUM CITRATE; ALPHA-TOCOPHEROL ACETATE; CELLULOSE GUM; CITRIC ACID; PENTYLENE GLYCOL; TRIETHOXYCAPRYLYLSILANE; PHENOXYETHANOL; FERROUS OXIDE; SQUALANE; ETHYLHEXYL METHOXYCRYLENE; ETHYLHEXYLGLYCERIN; MICA; NIACINAMIDE; POTASSIUM CETYL PHOSPHATE; DIETHYLHEXYL SYRINGYLIDENEMALONATE; ACACIA SENEGAL GUM; PALMITOYL TRIPEPTIDE-1; HYDROXYACETOPHENONE

Good Weather Skin The One Daily Sun Cream Warm Glow SPF 30

Active Ingredients

Zinc Oxide 15%

Purpose

Sunscreen

Uses

Helps prevent sunburn. If used as directed with other sun protection measures (see Directions), decreases the risk of skin cancer and early signs of aging caused by the sun.

Warnings

For external use only.

Do not use

on damaged or broken skin.

When using this product

keep out of eyes. Rinse with water to remove.

Stop use and ask a doctor if

rash occurs.

Keep out of reach of children.

If swallowed, get medical help or contact a Poison Control Center right away.

Directions

Apply liberally and evenly 15 min. before sun exposure. Reapply: after 40 minutes of swimming or sweating - immediately after towel drying - at least every 2 hours. Children under 6 months of age: Ask a doctor. Sun Protection Measures: Spending time in the sun increases your risk of skin cancer and early skin aging. To decrease this risk, regularly use a sunscreen with a Broad Spectrum SPF value of 15 or higher and other sun protection measures including: limiting time in the sun, especially from 10am-2pm, and wearing long-sleeve shirts, pants, hats, and sunglasses.

Other Information

Protect the product in this container from excessive heat and direct sun.

Inactive Ingredients

Water, caprylic/capric triglyceride, glycerin, squalane, butyloctyl salicylate, dicaprylyl carbonate, ethylhexyl methoxycrylene, pentylene glycol, cetearyl olivate, mica, polyhydroxystearic acid, glyceryl stearate citrate, hippophae rhamnoides oil, niacinamide, potassium cetyl phosphate, sorbitan olivate, palmitoyl tripeptide-1, palmitoyl tripeptide-7, triethoxycaprylylsilane, hydroxyacetophenone, inulin lauryl carbamate, iron oxide, polyglyceryl-3 methylglucose distearate, xanthan gum, diethylhexyl syringylidenemalonate, citric acid, trisodium ethylenediamine disuccinate, phenoxyethanol, acacia senegal gum, microcrystalline cellulose, lauroyl lysine, sodium stearoyl glutamate, ethylhexylglycerin, sodium citrate, tocopheryl acetate, cellulose gum.

Questions?

hello@goodweatherskin.com